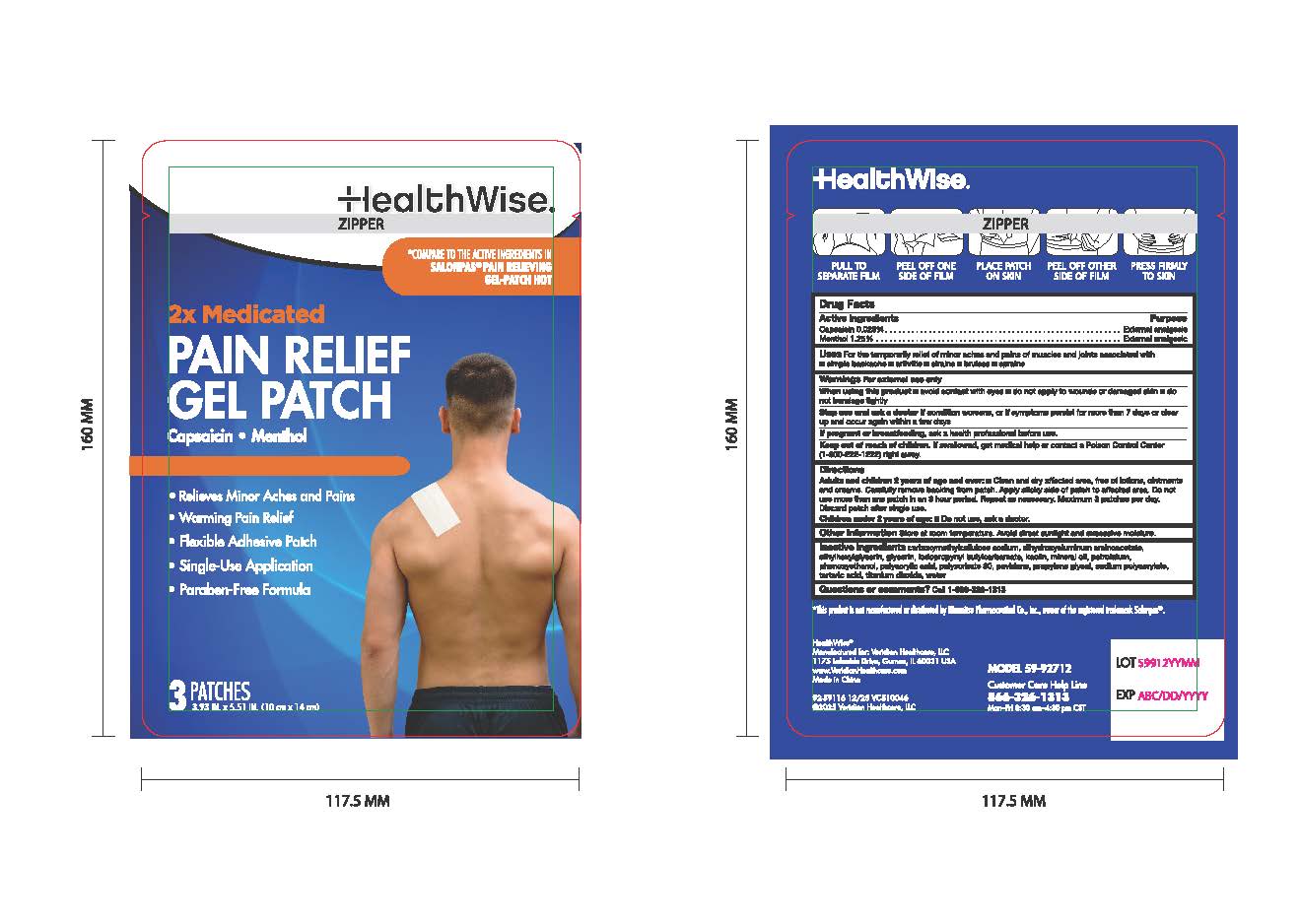 DRUG LABEL: HealthWise Pain Relief Gel Patch
NDC: 71101-105 | Form: PATCH
Manufacturer: Veridian Healthcare
Category: otc | Type: HUMAN OTC DRUG LABEL
Date: 20251208

ACTIVE INGREDIENTS: CAPSAICIN 0.025 g/100 g; MENTHOL 1.25 g/100 g
INACTIVE INGREDIENTS: CARBOXYMETHYLCELLULOSE SODIUM, UNSPECIFIED FORM; POLYACRYLIC ACID (8000 MW); PHENOXYETHANOL; TITANIUM DIOXIDE; GLYCERIN; SODIUM POLYACRYLATE (8000 MW); DIHYDROXYALUMINUM AMINOACETATE; MINERAL OIL; PETROLATUM; ETHYLHEXYLGLYCERIN; IODOPROPYNYL BUTYLCARBAMATE; WATER; KAOLIN; POVIDONE; TARTARIC ACID; POLYSORBATE 80; PROPYLENE GLYCOL

HealthWise Pain Relief Gel Patch

Active Ingredients

Capsaicin: 0.025%

Menthol 1.25%

Purpose

External analgesic

Uses

Temporary relief of minor aches and pains of muscles and joints associated with:

- simple backache
- arthritis
- strains
- bruises
- sprains

Warnings

For External Use Only

When using this product

- avoid contact with eyes
- do not apply to wounds or damage skin
- do not bandage tightly

Stop Use and ask a doctor if

- Conditions worsens
- Symptons persist for more than 7 days or clear up and occur again within a few days

If pregnant or breastfeeding

ask a health professional before use

Keep Out of Reach of Children

if swallowed, get medical help or contact Poison Control Center (1-800-222-1222) right away.

Directions for Use:

Adults and Childrens 12 Years of Age and over: Clean and dry affected area, free of lotions, ointments and creams. Carfully remove backing from patch. Apply sticky side of patch to affected area. Do not use more than one patch in an 8 hour period. Repeat as necessary. Maximum 3 patches per day. Discard partch after single use.

Children under 2 years of age:Do not use, ask a doctor

Inactive Ingredients:

carboxymethylcellulose sodium, dihydroxyaluminum aminoacetate, ethylhexylglycerin, glycerin, iodopropynyl butylcarbamate, kaolin, mineral oil, petrolatum, penoxyethanol, polyacrylic acid, polysorbate 80, povidone, propylene glycol, sodium polyacrylate, tartaric acid, titanium dioxide, water.

QUESTIONS

TOLL-FREE

Customer Care Help Line
866-326-1313